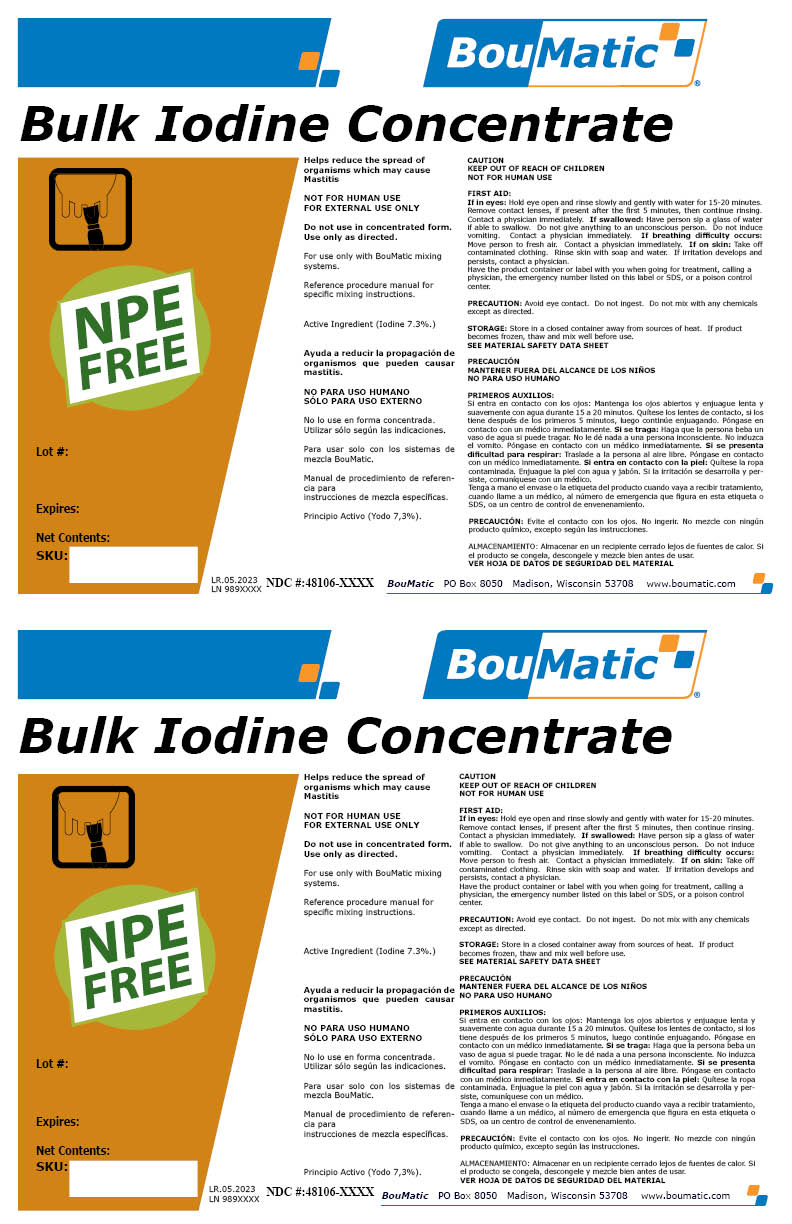 DRUG LABEL: Bulk Iodine Concentrate
NDC: 48106-2051 | Form: LIQUID
Manufacturer: BOUMATIC, LLC
Category: animal | Type: OTC ANIMAL DRUG LABEL
Date: 20230502

ACTIVE INGREDIENTS: IODINE 7.3 g/100 g
INACTIVE INGREDIENTS: WATER; ANHYDROUS CITRIC ACID; SODIUM CITRATE

Bulk Iodine Concentrate

Claim of effectiveness.

Helps reduce the spread of organisms
which may cause Mastitis

Use Directions

NOT FOR HUMAN USE
FOR EXTERNAL USE ONLY
Do not use in concentrated form.
Use only as directed.
For use only with BouMatic mixing
systems.
Reference procedure manual for
specific mixing instructions.

First Aid

If in eyes: Hold eye open and rinse slowly and gently with water for 15-20 minutes.
Remove contact lenses, if present after the first 5 minutes, then continue rinsing.
Contact a physician immediately. If swallowed: Have person sip a glass of water
if able to swallow. Do not give anything to an unconscious person. Do not induce
vomiting. Contact a physician immediately. If breathing difficulty occurs:
Move person to fresh air. Contact a physician immediately. If on skin: Take off
contaminated clothing. Rinse skin with soap and water. If irritation develops and
persists, contact a physician.
Have the product container or label with you when going for treatment, calling a
physician, the emergency number listed on this label or SDS, or a poison control
center.

Precautions & Hazards

PRECAUTION: Avoid eye contact. Do not ingest. Do not mix with any chemicals
except as directed.

STORAGE:

Store in a closed container away from sources of heat. If product
becomes frozen, thaw and mix well before use.